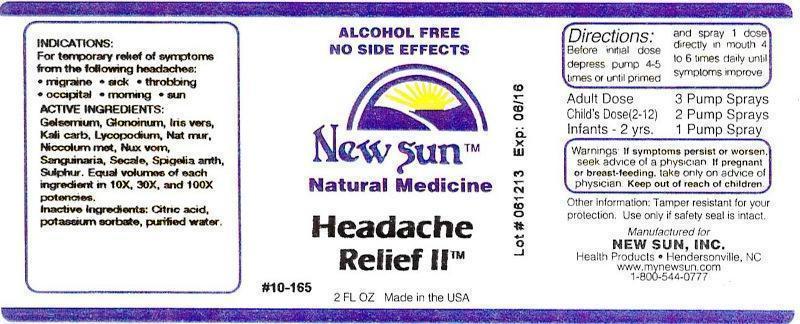 DRUG LABEL: Headache Relief II
NDC: 66579-0060 | Form: LIQUID
Manufacturer: New Sun Inc.
Category: homeopathic | Type: HUMAN OTC DRUG LABEL
Date: 20141024

ACTIVE INGREDIENTS: GELSEMIUM SEMPERVIRENS ROOT 10 [hp_X]/59 mL; NITROGLYCERIN 10 [hp_X]/59 mL; IRIS VERSICOLOR ROOT 10 [hp_X]/59 mL; POTASSIUM CARBONATE 10 [hp_X]/59 mL; LYCOPODIUM CLAVATUM SPORE 10 [hp_X]/59 mL; SODIUM CHLORIDE 10 [hp_X]/59 mL; NICKEL 10 [hp_X]/59 mL; STRYCHNOS NUX-VOMICA SEED 10 [hp_X]/59 mL; SANGUINARIA CANADENSIS ROOT 10 [hp_X]/59 mL; CLAVICEPS PURPUREA SCLEROTIUM 10 [hp_X]/59 mL; SPIGELIA ANTHELMIA 10 [hp_X]/59 mL; SULFUR 10 [hp_X]/59 mL
INACTIVE INGREDIENTS: CITRIC ACID MONOHYDRATE; POTASSIUM SORBATE; WATER

Headache Relief II

DOSAGE AND ADMINISTRATION

Directions: Before initial dose depress pump 4-5 times or until primed and spray 1 dose directly in mouth 4 to 6 times daily until symptoms improve.

Adult Dose: 3 Pump Sprays

Child's Dose (2-12): 2 Pump Sprays

Infants - 2 yrs. 1 Pump Spray

WARNINGS

Warnings: If symptoms persist or worsen, seek advice of a physician. If pregnant or breast-feeding, take only on advice of physician.

Keep out of reach of children.

Other information: Tamper resistant for your protection. Use only if safety seal is intact.

PURPOSE

Indications: For temporary relief of symptoms from the following headaches: •migraine •sick •throbbing •occipital •morning •sun

ACTIVE INGREDIENT

Active Ingredients: Gelsemium sempervirens, Glonoinum, Iris versicolor, Kali carbonicum, Lycopodium clavatum, Natrum muriaticum, Niccolum metallicum, Nux vomica, Sanguinaria canadensis, Secale cornutum, Spigelia anthelmia, Sulphur. Equal volumes of each ingredient in 10X, 30X, and 100X potencies.

Inactive Ingredient: Citric acid, potassium sorbate, purified water.

INDICATIONS AND USAGE

Indications: For temporary relief of symptoms from the following headaches:

- migraine
- sick
- throbbing
- occipital
- morning
- sun